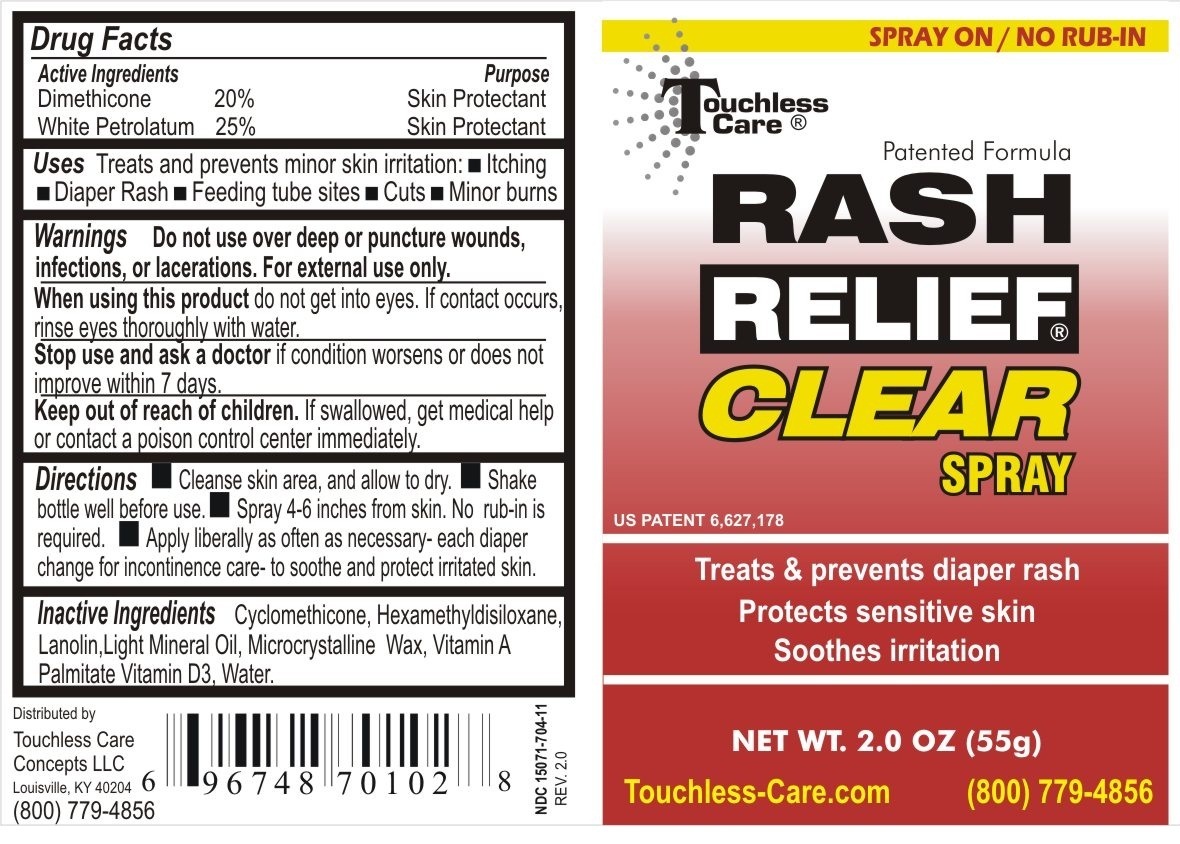 DRUG LABEL: Rash Relief Clear
NDC: 15071-704 | Form: LIQUID
Manufacturer: Touchless Care Concepts LLC
Category: otc | Type: HUMAN OTC DRUG LABEL
Date: 20111114

ACTIVE INGREDIENTS: Petrolatum 25 g/100 g; Dimethicone 20 g/100 g
INACTIVE INGREDIENTS: Mineral Oil; Cyclomethicone; Lanolin; Microcrystalline Wax; Hexamethyldisiloxane; Water; Cholecalciferol; Vitamin A Palmitate

RASH RELIEF CLEAR SPRAY

Active Ingredients

Dimethicone 20%

Petrolatum 25%

Purpose

Skin Protectant

Warnings

- Do not use over deep or puncture wounds, infections, or lacerations. For external use only.

- When using this product do not get into eyes. If contact occurs, rinse eyes throughout with water.

- Stop use and ask a doctor if condition worsens or does not improve with 7 days.

Directions

- Change wet and soiled diapers promptly, cleanse the diaper area, and allow to dry.

- Shake bottle well before use.

- Spray 4-6 inches from skin. No rub-in is required.

- Apply liberally as often as necessary, with each diaper change, and especially at bedtime or anytime exposure to we diapers is prolonged.

Inactive Ingredients

Cyclomethicone, Hexamethyldisiloxane, Lanolin, Light Mineral Oil, Microcrystalline Wax, Vitamin A Palmitate, Vitamin D3, Water

INDICATIONS AND USAGE

Uses: Protects minor skin irritation due to diaper rash and helps seal out wetness.

- Keep out of reach of children. If swallowed, get medical help or contact a local poison control center immediately.

PACKAGE LABEL

Enter section text here